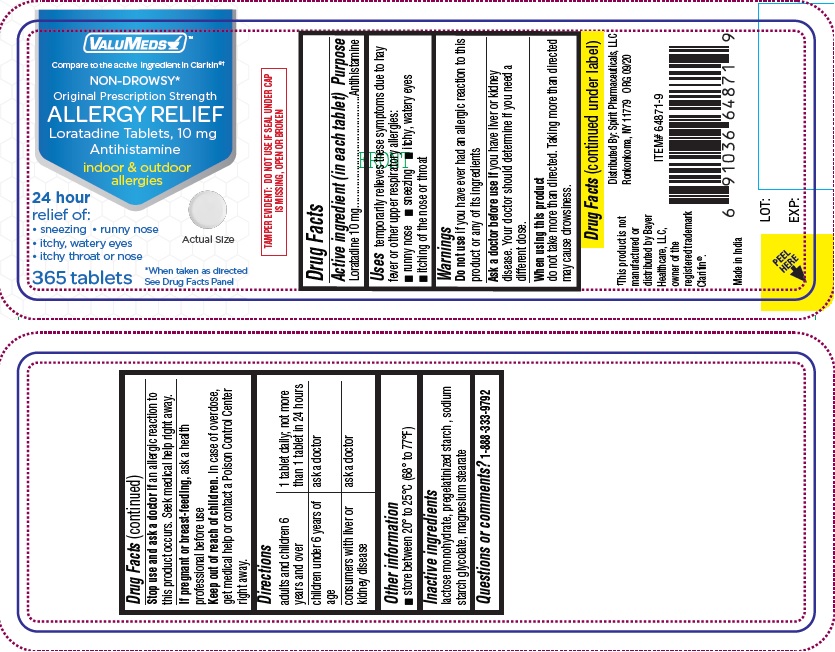 DRUG LABEL: Loratadine
NDC: 68210-4110 | Form: TABLET
Manufacturer: Spirit Pharmaceuticals LLC
Category: otc | Type: HUMAN OTC DRUG LABEL
Date: 20241213

ACTIVE INGREDIENTS: LORATADINE 10 mg/1 1
INACTIVE INGREDIENTS: LACTOSE MONOHYDRATE; STARCH, CORN; MAGNESIUM STEARATE; SODIUM STARCH GLYCOLATE TYPE A POTATO

Loratadine Tablets, 10 mg

Active ingredient

Loratadine 10 mg

Purpose

Antihistamine

Uses

temporarily relieves these symptoms due to hay fever or other upper respiratory allergies:

- runny nose
- sneezing
- itchy, water eyes
- itching of the nose or throat

Warnings

Do not use

if you have ever had an allergic reaction to this product or any of its ingredients

Ask a doctor before use if

you have liver or kidney disease. Your doctor should determine if you need a different dose.

When usung this product

do not take more than directed. Taking more than directed may cause drowsiness.

Stop use and ask a doctor if

an allergic reaction to this product occurs. Seek medical help right away.

If pregnant or breast-feeding,

ask a health professional before use

Keep out of reach of children

In case of overdose, get medical help or contact a Poison Control Center right away.

Directions

adults and children 6 years and over | 1 tablet daily; not more than 1 tablet in 24 hours
children under 6 years of age | ask a doctor
consumers with liver or kidney disease | ask a doctor

Other information

- Tamper-evident: do not use if foil under cap is missing, open or broken
- store between 20º to 25ºC (68º to 77ºF)

Inactive ingredients

Lactose monohydrate, magnesium stearate, sodium starch glycolate and starch maize pregelatinized

Questions or comments?

1-888-333-9792

PRINCIPAL DISPLAY PANEL

Compare to the active ingredient in Claritin®†

NON-DROWSY*
Original Prescription Strength
Loratadine Tablets, 10 mg / Antihistamine
Indoor & Outdoor Allergies
24 Hour Relief of: • Sneezing • Runny Nose • Itchy, Watery Eyes • Itchy Throat or Nose
365 Tablets
*When taken as directed
See Drug Facts Panel

†This product is not manufactured or distributed by Bayer Healthcare, LLC, owner of the registered trademark Claritin®.